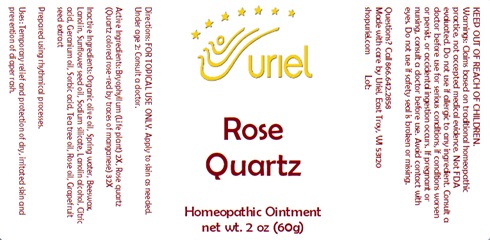 DRUG LABEL: Rose Quartz
NDC: 48951-8309 | Form: OINTMENT
Manufacturer: Uriel Pharmacy Inc.
Category: homeopathic | Type: HUMAN OTC DRUG LABEL
Date: 20241211

ACTIVE INGREDIENTS: SILICON DIOXIDE 32 [hp_X]/1 g; KALANCHOE DAIGREMONTIANA LEAF 2 [hp_X]/1 g
INACTIVE INGREDIENTS: SORBIC ACID; TEA TREE OIL; OLIVE OIL; WATER; YELLOW WAX; LANOLIN; SUNFLOWER OIL; SODIUM SILICATE; LANOLIN ALCOHOLS; CITRIC ACID MONOHYDRATE; GERANIUM OIL, ALGERIAN TYPE; ROSE OIL; CITRUS PARADISI SEED

Rose Quartz

INDICATIONS AND USAGE

Directions: FOR TOPICAL USE ONLY.

DOSAGE AND ADMINISTRATION

Apply to skin as needed. Under age 2: Consult a doctor.

ACTIVE INGREDIENT

Active Ingredients: Bryophyllum (Life plant) 2X, Rose quartz (Quartz colored rose-red by traces of manganese) 32X

INACTIVE INGREDIENT

Inactive Ingredients: Organic olive oil, Spring water, Beeswax, Lanolin, Sunflower seed oil, Sodium silicate, Lanolin alcohol, Citric acid, Geranium oil, Sorbic acid, Tea tree oil, Rose oil, Grapefruit seed extract

Prepared using rhythmical processes.

PURPOSE

Uses: Temporary relief and protection of dry, irritated skin and prevention of diaper rash.

KEEP OUT OF REACH OF CHILDREN.

Warnings: FOR EXTERNAL USE ONLY.
Claims based on traditional homeopathic practice, not accepted medical evidence. Not FDA evaluated. Do not use if allergic to any ingredient. Consult a doctor before use for serious conditions, if conditions worsen or persist, or accidental ingestion occurs. If pregnant or nursing, consult a doctor before use. Avoid contact with eyes. Do not use if safety seal is broken or missing.

Questions? Call 866.642.2858
Made with care by Uriel, East Troy, WI 53120
shopuriel.com Lot: